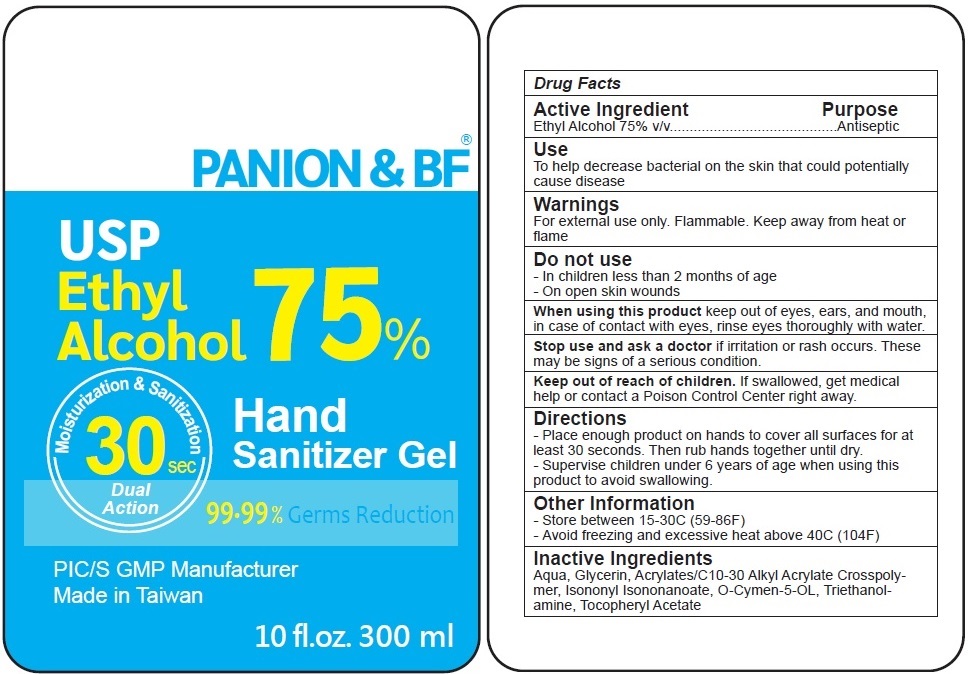 DRUG LABEL: PANION AND BF Hand Sanitizer
NDC: 78279-001 | Form: GEL
Manufacturer: PANION & BF BIOTECH INC.
Category: otc | Type: HUMAN OTC DRUG LABEL
Date: 20200701

ACTIVE INGREDIENTS: ALCOHOL 75 mL/100 mL
INACTIVE INGREDIENTS: WATER; GLYCERIN; CARBOMER INTERPOLYMER TYPE A (ALLYL SUCROSE CROSSLINKED); ISONONYL ISONONANOATE; O-CYMEN-5-OL; TROLAMINE; .ALPHA.-TOCOPHEROL ACETATE

PANION & BF® Hand Sanitizer Gel

Active Ingredient

Ethyl Alcohol 75% v/v

Purpose

Antiseptic

Use

To help decrease bacterial on the skin that could potentially cause disease

Warnings

For external use only. Flammable. Keep away from heat or flame

Do not use

- In children less than 2 months of age
- On open skin wounds

When using this product keep out of eyes, ears, and mouth, in case of contact with eyes,rinse eyes thoroughly with water.

Stop use and ask a doctor if irritation or rash occurs. These may be signs of a serious condition.

Keep out of reach of children. If swallowed, get medical help or contact a Poison Control Center right away.

Directions

- Place enough product on hands to cover all surfaces for at least 30 seconds. Then rub hands together until dry.

- Supervise children under 6 years of age when using this product to avoid swallowing.

Other Information

- Store between 15-30C (59-86F)

- Avoid freezing and excessive heat above 40C (104F)

Inactive Ingredients

Aqua, Glycerin, Acrylates/C10-30 Alkyl Acrylate Crosspolymer, Isononyl Isononanoate, O-Cymen-5-OL, Triethanolamine,Tocopheryl Acetate

USP

Moisturization & Sanitization

30 sec

Dual Action

99.99 % Germs Reduction

PIC/S GMP Manufacturer

Made in Taiwan